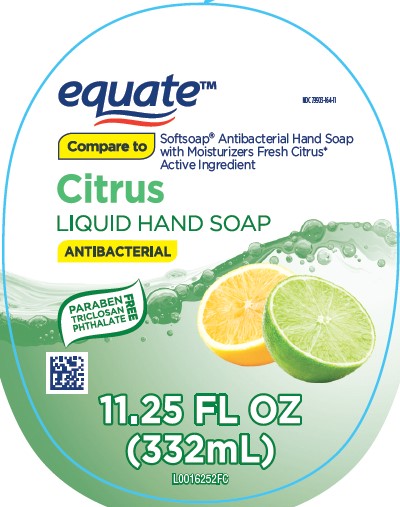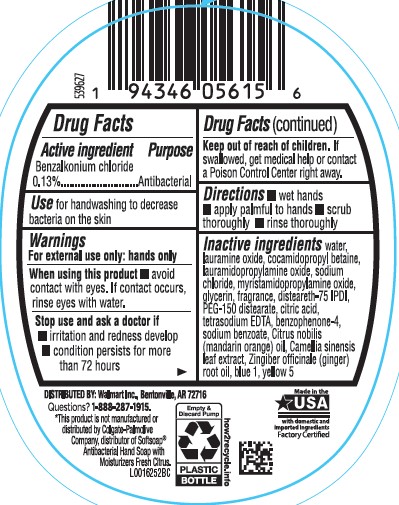 DRUG LABEL: Moisturizing Antibacterial
NDC: 79903-164 | Form: SOAP
Manufacturer: Walmart Inc.
Category: otc | Type: HUMAN OTC DRUG LABEL
Date: 20260227

ACTIVE INGREDIENTS: BENZALKONIUM CHLORIDE 1.3 mg/1 mL
INACTIVE INGREDIENTS: WATER; LAURAMINE OXIDE; COCAMIDOPROPYL BETAINE; LAURAMIDOPROPYLAMINE OXIDE; SODIUM CHLORIDE; MYRISTAMIDOPROPYLAMINE OXIDE; GLYCERIN; DISTEARETH-75 ISOPHORONE DIISOCYANATE; PEG-150 DISTEARATE; CITRIC ACID MONOHYDRATE; EDETATE SODIUM; SULISOBENZONE; SODIUM BENZOATE; MANDARIN OIL; GREEN TEA LEAF; GINGER OIL; FD&C BLUE NO. 1; FD&C YELLOW NO. 5

Equate 633.002/633AC
Antibacterial Hand Soap with Moisturizers – Fresh Citrus

Active Ingredient

Benzalkonium chloride 0.13%

Purpose

Antibacterial

Use

For handwashing to decrease bacteria on the skin

Warnings

For external use only: hands only

When using this product

- avoid contact with eyes. If contact occurs, rinse eyes thoroughly with water.

Stop use and ask a doctor if

- irritation and redness develop
- condition persists for more than 72 hours

Keep out of reach of children.

If swallowed, get medical help or contact a Poison Control Center right away.

Directions

- wet hands
- apply palmful to hands
- scrub thoroughly
- rinse thoroughly

Inactive ingredients

water, lauramine oxide, cocamidopropyl betaine, lauramidopropylamine oxide, sodium chloride, myristamidopropylamine oxide, glycerin, fragrance, disteareth-75 IPDI, PEG-150 distearate, citric acid, tetrasodium EDTA, benzophenone-4, sodium benzoate, Citrus nobilis (mandarin orange) oil, Camellia sinensis leaf extract, Zingiber officinale (ginger) root oil, blue 1, yellow 5

DISTRIBUTED BY: Walmart Inc., Bentonville, AR 72716

Questions? 1-888-287-1915

*This product is not manufactured or distributed by Colgate-Palmolive Company, distributor of Softsoap®Antibacterial Hand Soap with Moisturizers Fresh Citrus.

how2recycle.info

Empty & discard bottle

Plastic Bottle

Made in the USA with domestic and imported ingredients

Factory Certified

principal display panel

NDC 79903-164-11

equate™

Compare to Softsoap®Antibacterial Hand Soap with Moisturizers Fresh Citrus* active ingredient

Citrus

LIQUID HAND SOAP

ANTIBACTERIAL

Paraben, triclosan, phthalate free

11.25 FL OZ (332 mL)